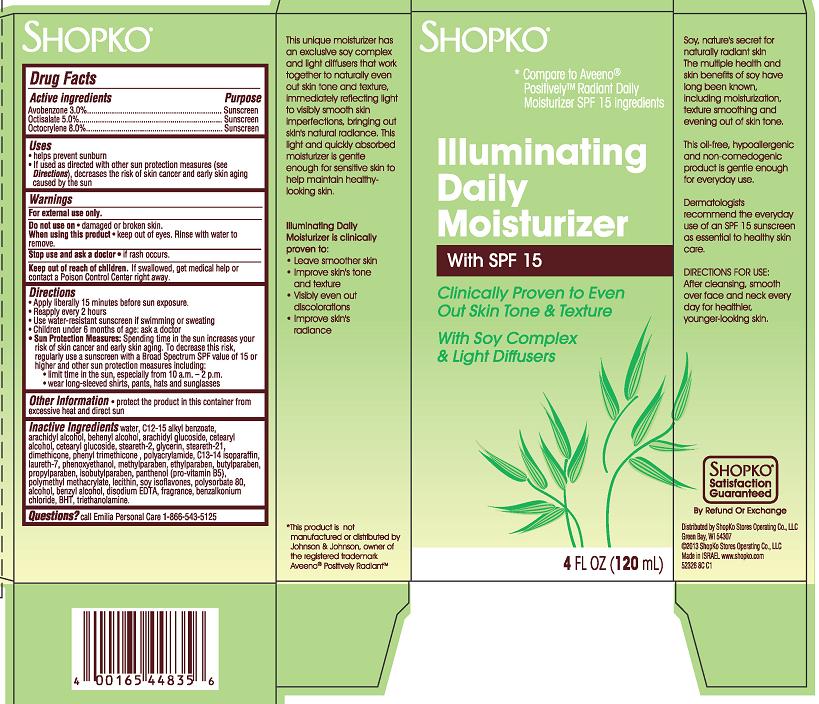 DRUG LABEL: ShopKo Illuminating Daily Moisturizer Broad Spectrum SPF15 Sunscreen
NDC: 37012-326 | Form: CREAM
Manufacturer: Shopko Stores Operating Co., LLC
Category: otc | Type: HUMAN OTC DRUG LABEL
Date: 20130508

ACTIVE INGREDIENTS: AVOBENZONE 3 mg/100 mL; OCTISALATE 5 mg/100 mL; OCTOCRYLENE 8 mg/100 mL
INACTIVE INGREDIENTS: WATER; ALKYL (C12-15) BENZOATE; ARACHIDYL ALCOHOL; DOCOSANOL; ARACHIDYL GLUCOSIDE; CETOSTEARYL ALCOHOL; CETEARYL GLUCOSIDE; STEARETH-2; GLYCERIN; STEARETH-21; DIMETHICONE; PHENYL TRIMETHICONE; POLYACRYLAMIDE (1500 MW); C13-14 ISOPARAFFIN; LAURETH-7; PHENOXYETHANOL; METHYLPARABEN; ETHYLPARABEN; BUTYLPARABEN; PROPYLPARABEN; ISOBUTYLPARABEN; PANTHENOL; LECITHIN, SOYBEAN; SOY ISOFLAVONES; POLYSORBATE 80; BENZYL ALCOHOL; EDETATE DISODIUM; BENZALKONIUM CHLORIDE; BUTYLATED HYDROXYTOLUENE; TROLAMINE; ALCOHOL

SHOPKO Illuminating Daily Moisturizer With SPF 15

Active ingredient

Avobenzone 3.0%

Oclisalate 5.0%

Octocrylene 8.0%

Purpose

Sunscreen

Uses

- helps prevent sunburn
- If used as directed with other sun protection measures (see Directions), decreases the risk of skin cancer and early skin aging caused by the sun

Warnings

For external use only.

Do not use on

- damaged or broken skin.

When using this product

- keep out of eyes. Rinse with water to remove.

Stop use and ask a doctor

- if rash occurs.

Keep Out of Reach of Children.

If swallowed, get medical help or contact a Poison Control Center right away.

Directions

- Apply liberally 15 minutes before sun exposure.
- Reapply every 2 hours
- Use water-resistant sunscreen if swimming or sweating
- Children under 6 months of age: ask a doctor
- Sun Protection Measures: Spending time in the sun increases your risk of skin cancer and early skin aging. To decrease this risk, regularly use a sunscreen with a Broad Spectrum SPF value of 15 or higher and other sun protection measures including:
  - limit time in the sun, especially from 10 a.m. - 2 p.m.
  - wear long-sleeved shirts, pants, hats and sunglasses

Other Information

- protect the product in this container from excessive heat and direct sun

Inactive Ingredients

water, C12-15 alkyl benzoate, arachidyl alcohol, beheynl alcohol, arachidyl glucoside, cetearyl alcohol, cetearyl glucoside, steareth-2, glycerin, steareth-21, dimethicone, phenyl trimethicone, polyacrylamide, C13-14 isoparaffin, laureth-7, phenoxyethanol, methylparaben, ethylparaben, butylparaben, propylparaben, isobutylparaben, panthenol (pro-vitamin B5), polymethyl methacrylate, lecithin, soy isoflavones, polysorbate 80, alcohol, benzyl alcohol, disodium EDTA, fragrance, benzalkonium chloride, BHT, triethanolamine.

Package/Label Principal Display Panel - Carton Label

Shopko*

*Compare to Aveeno® PositivelyTM Radiant Daily Moisturizer SPF 15 Ingredients

Illuminating Daily Moisturizer

With SPF 15

Clinically Proven to Even Out Skin Tone & Texture

With Soy Complex & Light Diffusers

4 FL OZ (120 mL)

Soy, nature's secret for naturally radiant skin
The multiple health and skin benefits of soy have long been know, including moisturization, texture smoothing and evening out of skin tone.

This oil-free, hypoallergenic and non-comedogenic product is gentle enough for everyday use.

Dermatologists recommend the everyday use of an SPF 15 sunscreen as essential to healthy skin care.

DIRECTIONS FOR USE:
After cleansing, smooth over face and neck every day for healthier, younger-looking skin.

This unique moisturizer has an exclusive soy complex and light diffusers that work together to naturally even out skin tone and texture. Immediately reflecting light to visibly smooth skin imperfections, bringing out skin's natural radiance. This light and quickly absorbed moisturizer is gentle enough for sensitive skin to help maintain healthy-looking skin.

Illuminating Daily Moisturizer is clinically proven to:

- Leave smoother skin
- Improve skin's tone and texture
- Visibly even out discolorations
- Improve skin's radiance

*This product is not manufactured or distributed by Johnson & Johnson, owner of the registered trademark Aveeno® Positively RadiantTM

SHOPKO* Satisfaction Guaranteed
By Refund or Exchange

Distributed by ShopKo Stores Operating Co., LLC
Green Bay, WI 54307
© 2013 ShopKo Stores Operating Co., LLC
Made in Israel. www.shopko.com

52326 8C C1

Carton Label